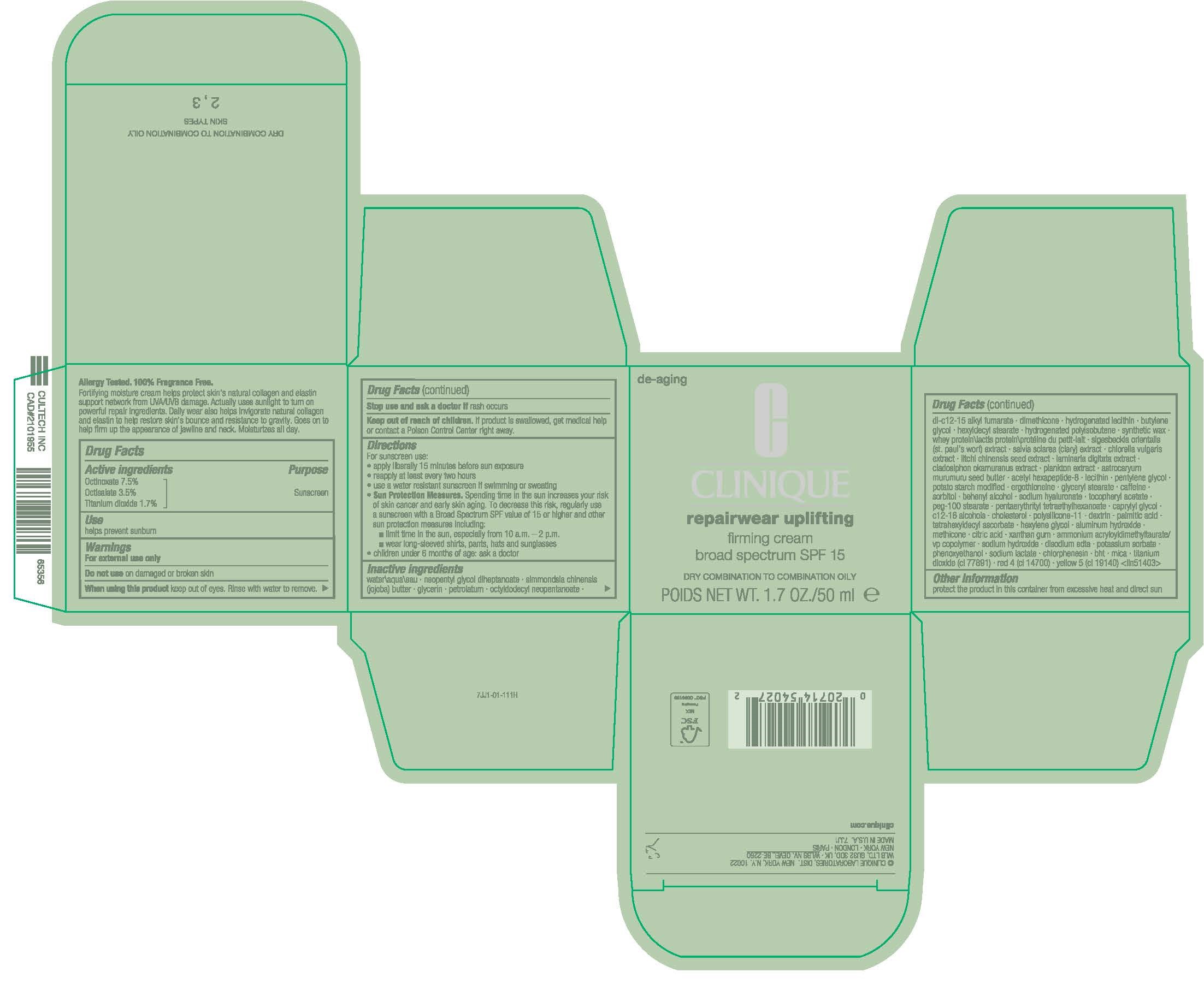 DRUG LABEL: REPAIRWEAR
NDC: 49527-017 | Form: CREAM
Manufacturer: CLINIQUE LABORATORIES LLC
Category: otc | Type: HUMAN OTC DRUG LABEL
Date: 20250414

ACTIVE INGREDIENTS: OCTINOXATE 75 mg/1 mL; OCTISALATE 35 mg/1 mL; TITANIUM DIOXIDE 17 mg/1 mL
INACTIVE INGREDIENTS: WATER; PETROLATUM; HIGH DENSITY POLYETHYLENE; GLYCERIN; OCTYLDODECYL NEOPENTANOATE; DI-C12-15 ALKYL FUMARATE; DIMETHICONE; BUTYLENE GLYCOL; HEXYLDECYL STEARATE; GLYCERYL MONOSTEARATE; PENTYLENE GLYCOL; CLARY SAGE; CHLORELLA VULGARIS; GUGGUL; LITCHI CHINENSIS SEED; LAMINARIA DIGITATA; CLADOSIPHON OKAMURANUS; ASTROCARYUM MURUMURU SEED BUTTER; SORBITOL; CAFFEINE; CHOLESTEROL; ACETYL HEXAPEPTIDE-8; HYALURONATE SODIUM; PEG-100 STEARATE; PENTAERYTHRITYL TETRAETHYLHEXANOATE; DOCOSANOL; .ALPHA.-TOCOPHEROL ACETATE; CAPRYLYL GLYCOL; C12-16 ALCOHOLS; MEDIUM-CHAIN TRIGLYCERIDES; ERGOTHIONEINE; ICODEXTRIN; PALMITIC ACID; AMMONIUM ACRYLOYLDIMETHYLTAURATE/VP COPOLYMER; TETRAHEXYLDECYL ASCORBATE; HEXYLENE GLYCOL; CITRIC ACID MONOHYDRATE; POTASSIUM SORBATE; XANTHAN GUM; ALUMINUM OXIDE; SODIUM HYDROXIDE; EDETATE DISODIUM; PHENOXYETHANOL; FD&C RED NO. 4; FD&C YELLOW NO. 5; MICA

REPAIRWEAR UPLIFTING FIRMING CREAM BROAD SPECTRUM SPF 15 DRY

Drug Facts

Active ingredients

Octinoxate 7.5%
Octisalate 3.5%
Titanium dioxide 1.7%

Purpose

Sunscreen

Use

helps prevent sunburn

Warnings

For external use only

Do not use on damaged or broken skin

When using this product keep out of eyes. Rinse with water to remove.

Stop use and ask a doctor if rash occurs

Keep out of reach of children. If product is swallowed, get medical help or contact a Poison Control Center right away.

Directions

For sunscreen use:

- apply liberally 15 minutes before sun exposure
- reapply at least every two hours
- use a water resistant sunscreen if swimming or sweating
- Sun Protection Measures. Spending time in the sun increases your risk of skin cancer and early skin aging. To decrease this risk, regularly use a sunscreen with a Broad Spectrum SPF value of 15 or higher and other sun protection measures including:
  - limit time in the sun, especially from 10 a.m. – 2 p.m.
  - wear long-sleeved shirts, pants, hats and sunglasses
- children under 6 months of age: ask a doctor

Inactive ingredients

water\aqua\eau • simmondsia chinensis (jojoba) butter • petrolatum • polyethylene • glycerin • octyldodecyl neopentanoate • di-c12-15 alkyl fumarate • dimethicone • hydrogenated lecithin • butylene glycol • hydrogenated polyisobutene • hexyldecyl stearate • glyceryl stearate • pentylene glycol • potato starch modified • sigesbeckia orientalis (st. paul's wort) extract • salvia sclarea (clary) extract • chlorella vulgaris extract • commiphora mukul resin extract • litchi chinensis seed extract • laminaria digitata extract • plankton extract • cladosiphon okamuranus extract • whey protein\lactis protein\protéine du petit-lait • astrocaryum murumuru seed butter • sorbitol • caffeine • cholesterol • lecithin • acetyl hexapeptide-8 • sodium hyaluronate • peg-100 stearate • pentaerythrityl tetraethylhexanoate • behenyl alcohol • tocopheryl acetate • caprylyl glycol • c12-16 alcohols • caprylic/capric triglyceride • ergothioneine • polysilicone-11 • methicone • dextrin • palmitic acid • ammonium acryloyldimethyltaurate/vp copolymer • tetrahexyldecyl ascorbate • hexylene glycol • citric acid • potassium sorbate • xanthan gum • alumina • sodium hydroxide • disodium edta • phenoxyethanol • red 4 (ci 14700) • yellow 5 (ci 19140) • titanium dioxide (ci 77891) • mica [iln39282]

Other information

protect the product in this container from excessive heat and direct sun

PRINCIPAL DISPLAY PANEL - 50 ml Jar Carton

CLINIQUE

repairwear uplifting

firming cream
broad spectrum SPF 15

VERY DRY TO DRY

POIDS NET WT. 1.7 OZ./50 ml e